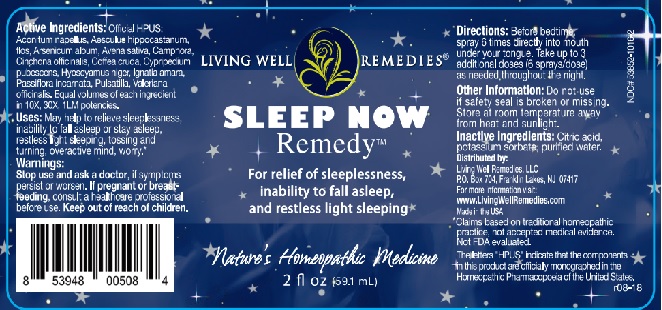 DRUG LABEL: Sleep Now Remedy
NDC: 53852-1016 | Form: LIQUID
Manufacturer: Living Well Remedies, LLC
Category: homeopathic | Type: HUMAN OTC DRUG LABEL
Date: 20181008

ACTIVE INGREDIENTS: AVENA SATIVA FLOWERING TOP 10 [hp_X]/59 mL; CAMPHOR (NATURAL) 10 [hp_X]/59 mL; ARABICA COFFEE BEAN 10 [hp_X]/59 mL; CYPRIPEDIUM PARVIFOLUM ROOT 10 [hp_X]/59 mL; STRYCHNOS IGNATII SEED 10 [hp_X]/59 mL; PASSIFLORA INCARNATA FLOWERING TOP 10 [hp_X]/59 mL; VALERIAN 10 [hp_X]/59 mL; ACONITUM NAPELLUS 10 [hp_X]/59 mL; HORSE CHESTNUT 10 [hp_X]/59 mL; ARSENIC TRIOXIDE 10 [hp_X]/59 mL; CINCHONA OFFICINALIS BARK 10 [hp_X]/59 mL; HYOSCYAMUS NIGER 10 [hp_X]/59 mL; PULSATILLA VULGARIS 10 [hp_X]/59 mL
INACTIVE INGREDIENTS: CITRIC ACID MONOHYDRATE; POTASSIUM SORBATE; WATER

Sleep Now Remedy

ACTIVE INGREDIENT

Active Ingredients: Official HPUS: Aconitum napellus, Aesculus hippocastanum, flos, Arsenicum album, Avena sativa, Camphora, Cinchona officinalis, Coffea cruda, Cypripedium pubescens, Hyoscyamus niger, Ignatia amara, Passiflora incarnata, Pulsatilla, Valeriana officinalis. Equal volumes of each ingredient in 10X, 30X, 1LM potencies.

*Claims based on traditional homeopathic practice, not accepted medical evidence.

Not FDA evaluated.

The letters "HPUS" indicate that the components in this product are officially monographed in the Homeopathic Pharmacopoeia of the United States.

INDICATIONS AND USAGE

Uses: May help to relieve sleeplessness, inability to fall asleep or stay asleep, restless light sleeping, tossing and turning, overactive mind, worry.*

WARNINGS

Warnings: Stop use and ask a doctor, if symptoms persist or worsen. If pregnant or breast-feeding, consult a healthcare professional before use.

Keep out of reach of children.

DOSAGE AND ADMINISTRATION

Directions: Before bedtime, spray 6 times directly into mouth under your tongue. Take up to 3 additional doses (6 sprays/dose) as needed throughout the night.

Other Information: Do not use if safety seal is broken or missing. Store at room temperature away from heat and sunlight.

Inactive ingredients: Citric acid, potassium sorbate, purified water.

QUESTIONS

Distributed by:

Living Well Remedies, LLC

P.O. Box 704, Franklin Lakes, NJ 07417

For more information visit:

www.LivingWellRemedies.com

Made in the USA

PACKAGE LABEL

LIVING WELL REMEDIES®

SLEEP NOW

Remedy™

For relief of sleeplesness,

inability to fall asleep,

and restless light sleeping

Nature's Homeopathic Medicine

2 fl oz (59.1mL)

PURPOSE

For relief of sleeplessness,

inability to fall asleep,

and restless light sleeping